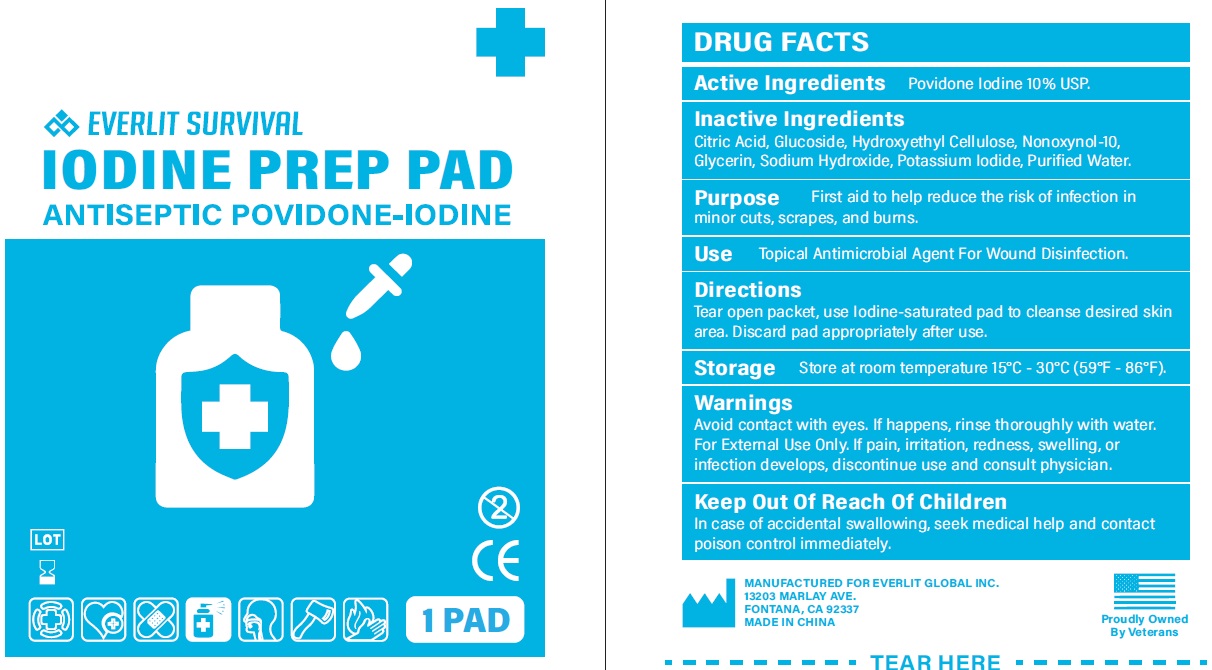 DRUG LABEL: Iodine Prep Pad Antiseptic
NDC: 72459-017 | Form: SOLUTION
Manufacturer: Yiwu Ori-Power Medtech Co.,Ltd.
Category: otc | Type: HUMAN OTC DRUG LABEL
Date: 20260101

ACTIVE INGREDIENTS: POVIDONE-IODINE 100 mg/1 g
INACTIVE INGREDIENTS: CITRIC ACID MONOHYDRATE; .BETA.-D-GLUCOPYRANOSE; HYDROXYETHYL CELLULOSE, UNSPECIFIED; NONOXYNOL-10; GLYCERIN; SODIUM HYDROXIDE; POTASSIUM IODIDE; WATER

EVERLIT SURVIVAL Iodine Prep Pad Antiseptic Povidone-Iodine

Active Ingredients

Povidone Iodine 10% USP.

Purpose

First aid to help reduce the risk of infection in minor cuts, scrapes, and burns.

Inactive Ingredients

Citric Acid, Glucoside, Hydroxyethyl Cellulose, Nonoxynol-10, Glycerin, Sodium Hydroxide, Potassium Iodide, Purified Water.

Use

Topical Antimicrobial Agent For Wound Disinfection.

Directions

Tear open packet, use Iodine-saturated pad to cleanse desired skin area. Discard pad appropriately after use.

Storage

Store at room temperature 15°C - 30°C (59°F - 86°F).

Warnings

Avoid contact with eyes. If happens, rinse thoroughly with water. For External Use Only. If pain, irritation, redness, swelling, or infection develops, discontinue use and consult physician.

Keep Out Of Reach Of Children

In case of accidental swallowing, seek medical help and contact poison control immediately.